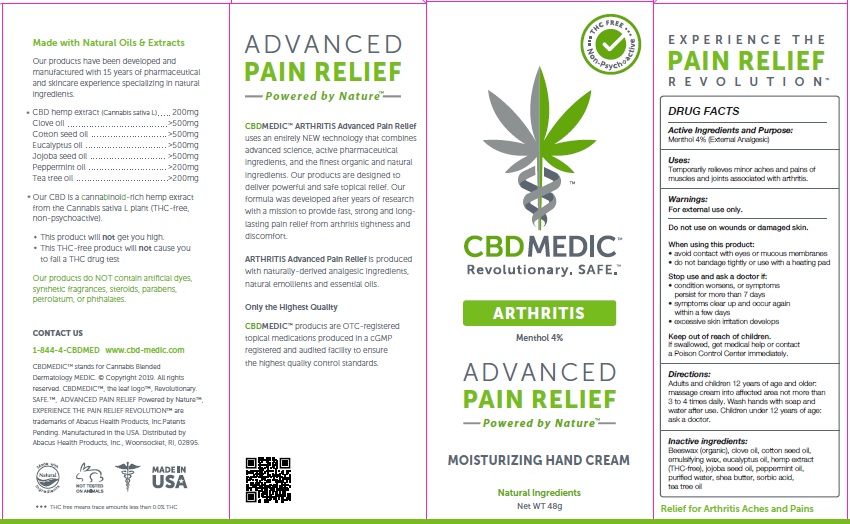 DRUG LABEL: CBDMEDIC Arthritis Pain Relief
NDC: 24909-740 | Form: CREAM
Manufacturer: AIDANCE SKINCARE & TOPICAL SOLUTIONS, LLC
Category: otc | Type: HUMAN OTC DRUG LABEL
Date: 20190312

ACTIVE INGREDIENTS: MENTHOL 40 mg/1 g
INACTIVE INGREDIENTS: WHITE WAX; CLOVE OIL; COTTONSEED OIL; CETOSTEARYL ALCOHOL; EUCALYPTUS OIL; HEMP; JOJOBA OIL; PEPPERMINT OIL; WATER; SHEA BUTTER; SORBIC ACID; TEA TREE OIL

CBDMEDIC Arthritis Pain Relief

Active Ingredient and Purpose

Menthol 4% (External Analgesic)

Uses

Temporarily relieves minor aches and pains of muscles and joints associated with arthritis.

Warnings

For external use only. Do not use on wounds or damaged skin. When using this product: • avoid contact with eyes or mucous membranes • do not bandage tightly or use with a heating pad. Stop use and ask a doctor if: • condition worsens, or symptoms persist for more than 7 days • symptoms clear up and occur again within a few days • excessive skin irritation develops.

Keep out of reach of children

If swallowed, get medical help or contact a poison control center immediately.

Directions

Adults and children 12 years of age and older: massage cream into affected area not more than 3 to 4 times daily. Wash hands with soap and water after use. Children under 12 years of age: ask a doctor.

Inactive ingredients

Beeswax (organic), clove oil, cotton seed oil, emulsifying wax, eucalyptus oil, hemp extract (THC-free), jojoba seed oil, peppermint oil, purified water, shea butter, sorbic acid, tea tree oil